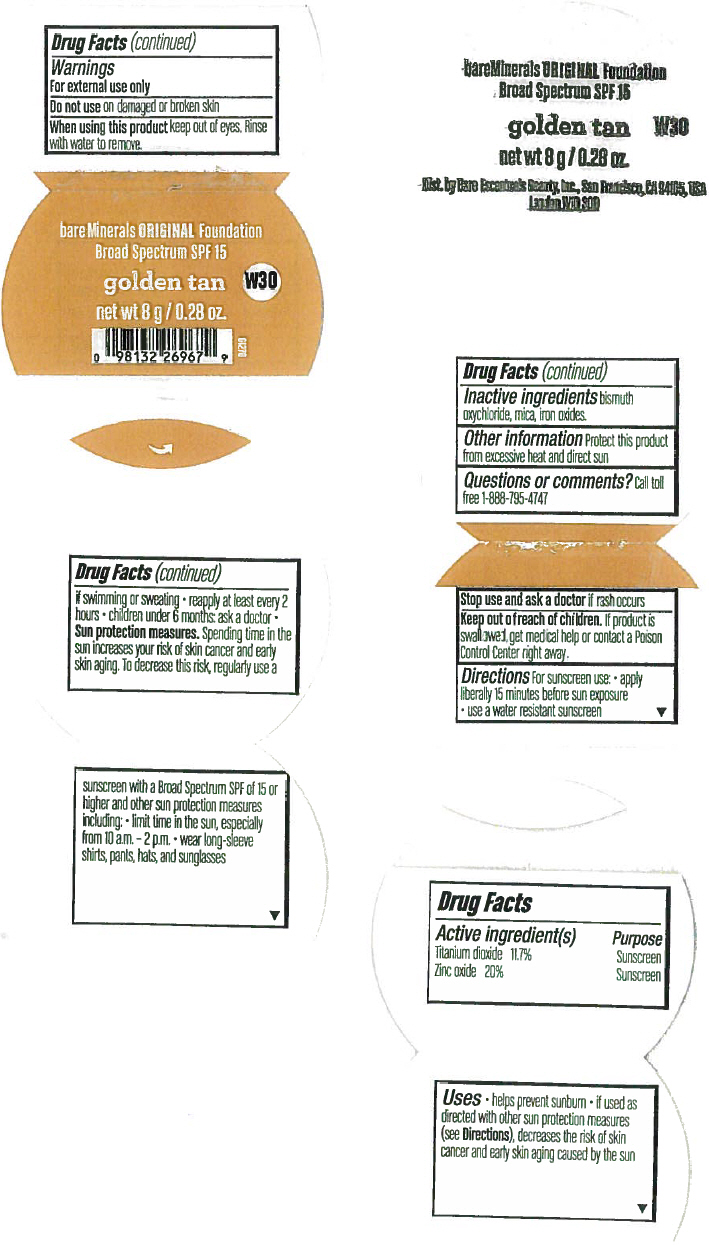 DRUG LABEL: Golden Tan Original
NDC: 98132-147 | Form: POWDER
Manufacturer: Bare Escentuals Beauty Inc.
Category: otc | Type: HUMAN OTC DRUG LABEL
Date: 20140402

ACTIVE INGREDIENTS: Titanium Dioxide 11.7 g/100 g; Zinc Oxide 20 g/100 g
INACTIVE INGREDIENTS: Bismuth Oxychloride; Ferric Oxide Red; Mica

Golden Tan Original

Drug Facts

Active Ingredients

Titanium Dioxide 11.7%

Zinc oxide 20%

Purpose

Sunscreen

Uses

Helps prevent sunburn. If used as directed with other sun protection measures (see Directions), decreases the risk of skin cancer and early skin aging caused by the sun.

Warnings

For external use only

Do not use on damaged or broken skin.

When using this product: Keep out of Eyes ; Rinse with water to remove

Stop use and ask a doctor if rash occurs.

Keep out of reach of children. If swallowed, get medical help or contact a Poison Control Center right away.

Directions

For sunscreen use:

Apply liberally 15 minutes before sun exposure

Use a water resistant sunscreen if swimming or sweating

Reapply at least every 2 hours

Children under 6 months, ask a doctor.

Sun protection measures. Spending time in the sun increases your risk of skin cancer and early skin aging. To decrease this risk, regularly use a sunscreen with a Broad Spectrum SPF of 15 or higher and other sun protection measures including: limit time in the sun, especially from 10am to 2 pm, wear long-sleeve shirts, pants, hats, and sunglasses.

Inactive Ingredients

Bismuth oxychloride, mica, iron oxides.

Other information

Protect this product from excessive heat and direct sun

Questions or comments?

Call toll free 1-888-795-4747

Bare Escentuals
MADE IN USA
Distr. By Bare Escentuals Beauty Inc., San Francisco CA 94104 USA
London W10 3QB

PRINCIPAL DISPLAY PANEL - 8 g Jar Label

bareMinerals ORIGINAL Foundation
Broad Spectrum SPF 15

golden tan

W30

net wt 8 g / 0.28 oz.